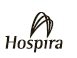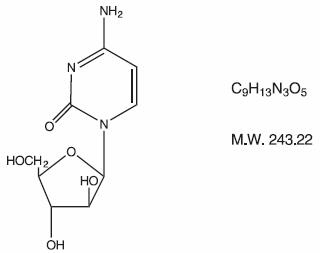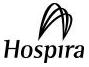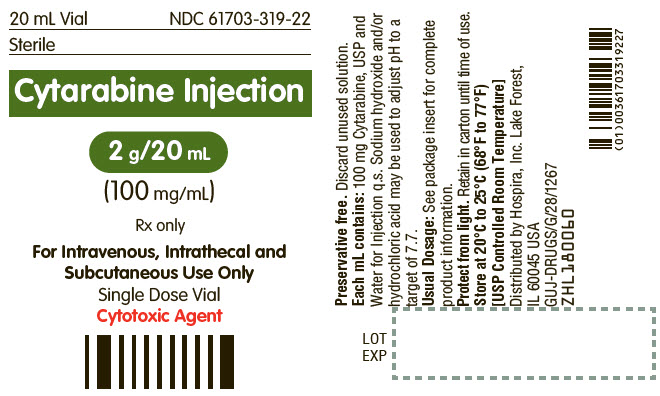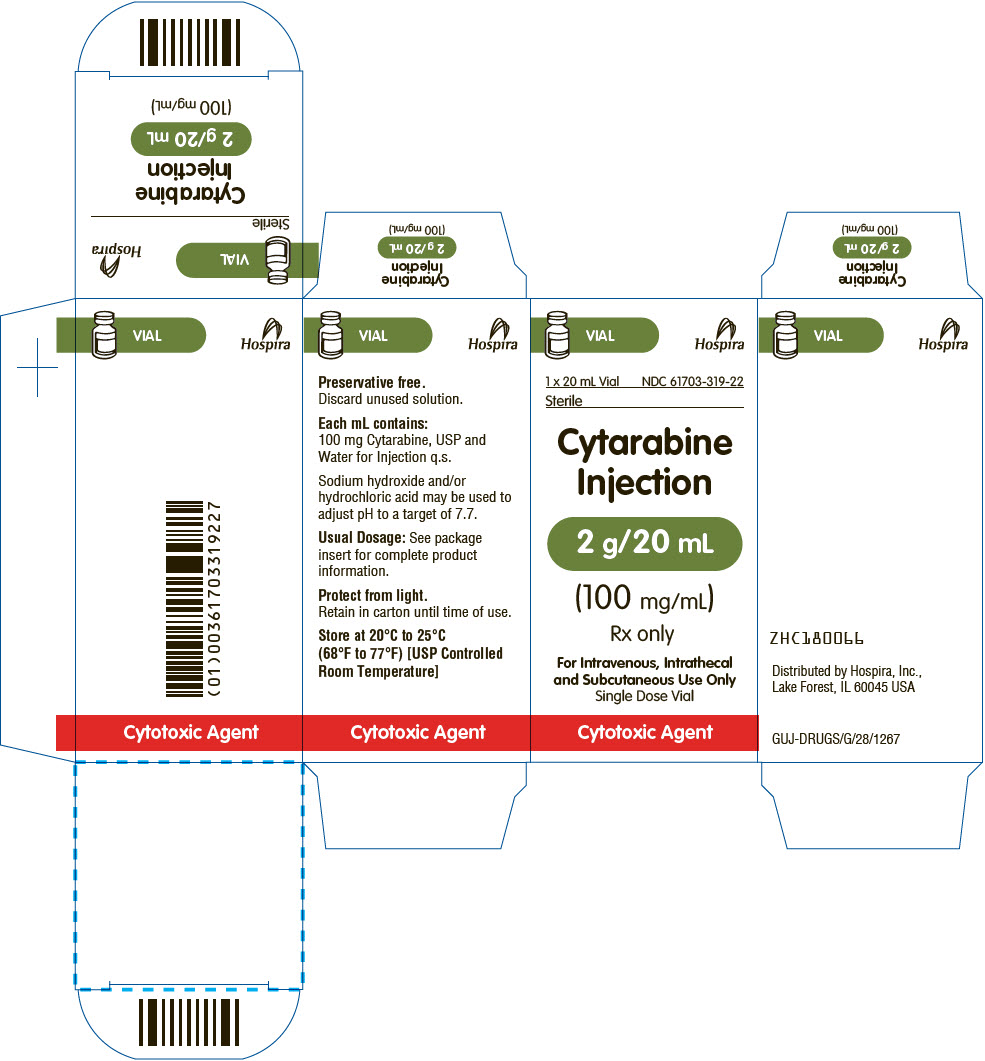 DRUG LABEL: Cytarabine
NDC: 61703-319 | Form: INJECTION, SOLUTION
Manufacturer: Hospira, Inc.
Category: prescription | Type: HUMAN PRESCRIPTION DRUG LABEL
Date: 20250813

ACTIVE INGREDIENTS: CYTARABINE 100 mg/1 mL
INACTIVE INGREDIENTS: WATER; HYDROCHLORIC ACID; SODIUM HYDROXIDE

Cytarabine Injection
For Intravenous, Intrathecal and Subcutaneous Use Only

Rx only

WARNING

Only physicians experienced in cancer chemotherapy should use Cytarabine Injection.

For induction therapy patients should be treated in a facility with laboratory and supportive resources sufficient to monitor drug tolerance and protect and maintain a patient compromised by drug toxicity. The main toxic effect of cytarabine injection is bone marrow suppression with leukopenia, thrombocytopenia and anemia. Less serious toxicity includes nausea, vomiting, diarrhea and abdominal pain, oral ulceration, and hepatic dysfunction.

The physician must judge possible benefit to the patient against known toxic effects of this drug in considering the advisability of therapy with Cytarabine Injection. Before making this judgement or beginning treatment, the physician should be familiar with the following text.

DESCRIPTION

Cytarabine Injection, an antineoplastic, is a sterile solution of cytarabine for intravenous, intrathecal or subcutaneous administration. Each mL contains 100 mg Cytarabine (100 mg/mL) in a 20 mL single dose vial (2 g/20 mL).

Cytarabine Injection 2 g/20 mL is a sterile solution for intravenous, intrathecal or subcutaneous administration. Each mL contains 100 mg Cytarabine, USP, and the following inactive ingredients: Water for Injection q.s. When necessary the pH is adjusted with hydrochloric acid and/or sodium hydroxide to a pH of 7.7.

Cytarabine is chemically 1-β-D-Arabinofuranosylcytosine. The structural formula is:

Cytarabine is an odorless, white to off-white crystalline powder which is freely soluble in water and slightly soluble in alcohol and in chloroform.

CLINICAL PHARMACOLOGY

Cell Culture Studies

Cytarabine is cytotoxic to a wide variety of proliferating mammalian cells in culture. It exhibits cell phase specificity, primarily killing cells undergoing DNA synthesis (S-phase) and under certain conditions blocking the progression of cells from the G1 phase to the S-phase. Although the mechanism of action is not completely understood, it appears that cytarabine acts through the inhibition of DNA polymerase. A limited, but significant, incorporation of cytarabine into both DNA and RNA has also been reported. Extensive chromosomal damage, including chromatoid breaks, have been produced by cytarabine and malignant transformation of rodent cells in culture has been reported. Deoxycytidine prevents or delays (but does not reverse) the cytotoxic activity.

Cellular Resistance and Sensitivity

Cytarabine is metabolized by deoxycytidine kinase and other nucleotide kinases to the nucleotide triphosphate, an effective inhibitor of DNA polymerase; it is inactivated by a pyrimidine nucleoside deaminase, which converts it to the non-toxic uracil derivative. It appears that the balance of kinase and deaminase levels may be an important factor in determining sensitivity or resistance of the cell to cytarabine.

Human Pharmacology

Cytarabine is rapidly metabolized and is not effective orally; less than 20 percent of the orally administered dose is absorbed from the gastrointestinal tract.

Following rapid intravenous injection of cytarabine labeled with tritium, the disappearance from plasma is biphasic. There is an initial distributive phase with a half-life of about 10 minutes, followed by a second elimination phase with a half-life of about 1 to 3 hours. After the distributive phase, more than 80 percent of plasma radioactivity can be accounted for by the inactive metabolite 1-β-D-arabinofuranosyluracil (ara-U). Within 24 hours about 80 percent of the administered radioactivity can be recovered in the urine, approximately 90 percent of which is excreted as ara-U.

Relatively constant plasma levels can be achieved by continuous intravenous infusion.

After subcutaneous or intramuscular administration of cytarabine labeled with tritium, peak-plasma levels of radioactivity are achieved about 20 to 60 minutes after injection and are considerably lower than those after intravenous administration.

Cerebrospinal fluid levels of cytarabine are low in comparison to plasma levels after single intravenous injection. However, in one patient in whom cerebrospinal fluid levels are examined after 2 hours of constant intravenous infusion, levels approached 40 percent of the steady state plasma level. With intrathecal administration, levels of cytarabine in the cerebrospinal fluid declined with a first order half-life of about 2 hours. Because cerebrospinal fluid levels of deaminase are low, little conversion to ara-U was observed.

Immunosuppressive Action

Cytarabine injection is capable of obliterating immune responses in man during administration with little or no accompanying toxicity. Suppression of antibody responses to E-coli-VI antigen and tetanus toxoid have been demonstrated. This suppression was obtained during both primary and secondary antibody responses.

Cytarabine injection also suppressed the development of cell-mediated immune responses such as delayed hypersensitivity skin reaction to dinitrochlorobenzene. However, it had no effect on already established delayed hypersensitivity reactions.

Following 5-day courses of intensive therapy with cytarabine injection the immune response was suppressed, as indicated by the following parameters: macrophage ingress into skin windows; circulating antibody response following primary antigenic stimulation; lymphocyte blastogenesis with phytohemagglutinin. A few days after termination of therapy there was a rapid return to normal.

INDICATIONS AND USAGE

Cytarabine Injection in combination with other approved anti-cancer drugs is indicated for remission induction in acute non-lymphocytic leukemia of adults and pediatric patients. It has also been found useful in the treatment of acute lymphocytic leukemia and the blast phase of chronic myelocytic leukemia. Intrathecal administration of Cytarabine Injection (preservative free preparations only) is indicated in the prophylaxis and treatment of meningeal leukemia.

CONTRAINDICATIONS

Cytarabine Injection is contraindicated in those patients who are hypersensitive to the drug.

WARNINGS

(See boxed WARNING)

Cytarabine is a potent bone marrow suppressant. Therapy should be started cautiously in patients with pre-existing drug-induced bone marrow suppression. Patients receiving this drug must be under close medical supervision and, during induction therapy, should have leucocyte and platelet counts performed daily. Bone marrow examinations should be performed frequently after blasts have disappeared from the peripheral blood. Facilities should be available for management of complications, possibly fatal, of bone marrow suppression (infection resulting from granulocytopenia and other impaired body defenses, and hemorrhage secondary to thrombocytopenia). One case of anaphylaxis that resulted in acute cardiopulmonary arrest and required resuscitation has been reported. This occurred immediately after the intravenous administration of cytarabine injection.

Severe and at times fatal CNS, GI and pulmonary toxicity (different from that seen with conventional therapy regimens of cytarabine injection) has been reported following some experimental dose schedules for cytarabine injection. These reactions include reversible corneal toxicity, and hemorrhagic conjunctivitis, which may be prevented or diminished by prophylaxis with a local corticosteroid eye drop; cerebral and cerebellar dysfunction, including personality changes, somnolence and coma, usually reversible; severe gastrointestinal ulceration, including pneumatosis cystoides intestinalis leading to peritonitis; sepsis and liver abscess; pulmonary edema, liver damage with increased hyperbilirubinemia; bowel necrosis; and necrotizing colitis. Rarely, severe skin rash, leading to desquamation has been reported. Complete alopecia is more commonly seen with experimental high dose therapy than with standard treatment programs using cytarabine injection. If experimental high dose therapy is used, do not use a preparation containing benzyl alcohol.

Cases of cardiomyopathy with subsequent death have been reported following experimental high dose therapy with cytarabine in combination with cyclophosphamide when used for bone marrow transplant preparation.

A syndrome of sudden respiratory distress, rapidly progressing to pulmonary edema and radiographically pronounced cardiomegaly has been reported following experimental high dose therapy with cytarabine used for the treatment of relapsed leukemia from one institution in 16/72 patients. The outcome of this syndrome can be fatal.

Two patients with childhood acute myelogenous leukemia who received intrathecal and intravenous cytarabine injection at conventional doses (in addition to a number of other concomitantly administered drugs) developed delayed progressive ascending paralysis resulting in death in one of the two patients.

Use in Pregnancy

Cytarabine Injection can cause fetal harm when administered to a pregnant woman. Cytarabine causes abnormal cerebellar development in the neonatal hamster and is teratogenic to the rat fetus. There are no adequate and well-controlled studies in pregnant women. Women of childbearing potential should be advised to avoid becoming pregnant.

A review of the literature has shown 32 reported cases where cytarabine injection was given during pregnancy, either alone or in combination with other cytotoxic agents:

Eighteen normal infants were delivered. Four of these had first trimester exposure. Five infants were premature or of low birth weight. Twelve of the 18 normal infants were followed up at ages ranging from six weeks to seven years, and showed no abnormalities. One apparently normal infant died at 90 days of gastroenteritis.

Two cases of congenital abnormalities have been reported, one with upper and lower distal limb defects, and the other with extremity and ear deformities. Both of these cases had first trimester exposure.

There were seven infants with various problems in the neonatal period, including pancytopenia, transient depression of WBC, hematocrit or platelets; electrolyte abnormalities; transient eosinophilia; and one case of increased lgM levels and hyperpyrexia possibly due to sepsis. Six of the seven infants were also premature. The child with pancytopenia died at 21 days of sepsis.

Therapeutic abortions were done in five cases. Four fetuses were grossly normal, but one had an enlarged spleen and another showed Trisomy C chromosome abnormality in the chorionic tissue.

Because of the potential for abnormalities with cytotoxic therapy, particularly during the first trimester, a patient who is or who may become pregnant while on cytarabine should be apprised of the potential risk to the fetus and the advisability of pregnancy continuation. There is a definite, but considerably reduced risk if therapy is initiated during the second or third trimester. Although normal infants have been delivered to patients treated in all three trimesters of pregnancy, follow-up of such infants would be advisable.

PRECAUTIONS

General Precautions

Patients receiving Cytarabine Injection must be monitored closely. Frequent platelet and leucocyte counts and bone marrow examinations are mandatory. Consider suspending or modifying therapy when drug-induced marrow depression has resulted in a platelet count under 50,000 or a polymorphonuclear granulocyte count under 1000/mm^3. Counts of formed elements in the peripheral blood may continue to fall after the drug is stopped and reach lowest values after drug-free intervals of 12 to 24 days. When indicated, restart therapy when definite signs of marrow recovery appear (on successive bone marrow studies). Patients whose drug is withheld until "normal" peripheral blood values are attained may escape from control.
When large intravenous doses are given too quickly, patients are frequently nauseated and may vomit for several hours post-injection. This problem tends to be less severe when the drug is infused.
The human liver apparently detoxifies a substantial fraction of an administered dose. In particular, patients with renal or hepatic function impairment may have a higher likelihood of CNS toxicity after high-dose cytarabine injection treatment. Use the drug with caution and possibly at reduced dose in patients whose liver or kidney function is poor.
Periodic checks of bone marrow, liver and kidney functions should be performed in patients receiving cytarabine injection.
Like other cytotoxic drugs, Cytarabine Injection may induce hyperuricemia secondary to rapid lysis of neoplastic cells. The clinician should monitor the patient's blood uric acid level and be prepared to use such supportive and pharmacologic measures as might be necessary to control this problem.
Acute pancreatitis has been reported to occur in a patient receiving Cytarabine Injection by continuous infusion and in patients being treated with Cytarabine Injection who have had prior treatment with L-asparaginase.

Information for Patients

Not applicable.

Laboratory Tests

See General Precautions.

Drug Interactions

Reversible decreases in steady-state plasma digoxin concentrations and renal glycoside excretion were observed in patients receiving beta-acetyldigoxin and chemotherapy regimens containing cyclophosphamide, vincristine and prednisone with or without cytarabine injection or procarbazine.

Steady-state plasma digitoxin concentrations did not appear to change. Therefore, monitoring of plasma digoxin levels may be indicated in patients receiving similar combination chemotherapy regimens. The utilization of digitoxin for such patients may be considered as an alternative.

An in vitro interaction study between gentamicin and cytarabine showed a cytarabine related antagonism for the susceptibility of K. pneumoniae strains. This study suggests that in patients on cytarabine being treated with gentamicin for a K. pneumoniae infection, the lack of a prompt therapeutic response may indicate the need for re-evaluation of antibacterial therapy.

Clinical evidence in one patient showed possible inhibition of fluorocytosine efficacy during therapy with cytarabine injection. This may be due to potential competitive inhibition of its uptake.

Carcinogenesis, Mutagenesis, Impairment of Fertility

Extensive chromosomal damage, including chromatoid breaks have been produced by cytarabine and malignant transformation of rodent cells in culture has been reported.

Pregnancy

See WARNINGS.

Labor and Delivery

Not applicable.

Nursing Mothers

It is not known whether this drug is excreted in human milk. Because many drugs are excreted in human milk and because of the potential for serious adverse reactions in nursing infants from cytarabine, a decision should be made whether to discontinue nursing or to discontinue the drug, taking into account the importance of the drug to the mother.

Pediatric Use

See INDICATIONS AND USAGE.

ADVERSE REACTIONS

Expected Reactions

Because cytarabine is a bone marrow suppressant, anemia, leukopenia, thrombocytopenia, megaloblastosis and reduced reticulocytes can be expected as a result of administration with Cytarabine Injection. The severity of these reactions are dose and schedule dependent. Cellular changes in the morphology of bone marrow and peripheral smears can be expected.

Following 5-day constant infusions or acute injections of 50 mg/m^2 to 600 mg/m^2, white cell depression follows a biphasic course. Regardless of initial count, dosage level, or schedule, there is an initial fall starting the first 24 hours with a nadir at days 7-9. This is followed by a brief rise which peaks around the twelfth day. A second and deeper fall reaches nadir at days 15-24. Then there is a rapid rise to above baseline in the next 10 days. Platelet depression is noticeable at 5 days with a peak depression occurring between days 12-15. Thereupon, a rapid rise to above baseline occurs in the next 10 days.

Infectious Complications

Injection: Viral, bacterial, fungal, parasitic, or saprophytic infections, in any location in the body may be associated with the use of cytarabine injection alone or in combination with other immunosuppressive agents following immunosuppressant doses that affect cellular or humoral immunity. These infections may be mild, but can be severe and at times fatal.

The Cytarabine (Ara-C) Syndrome

A cytarabine syndrome has been described by Castleberry. It is characterized by fever, myalgia, bone pain, occasionally chest pain, maculopapular rash, conjunctivitis and malaise. It usually occurs 6-12 hours following drug administration. Corticosteroids have been shown to be beneficial in treating or preventing this syndrome. If the symptoms of the syndrome are deemed treatable, corticosteroids should be contemplated as well as continuation of therapy with Cytarabine Injection.

Most Frequent Adverse Reactions

anorexia | oral and anal inflammation | rash
nausea | or ulceration | thrombophlebitis
vomiting | hepatic dysfunction | bleeding (all sites)
diarrhea | fever

Nausea and vomiting are most frequent following rapid intravenous injection.

Less Frequent Adverse Reactions

sepsis | sore throat | conjunctivitis (may occur with rash)
pneumonia | esophageal ulceration | dizziness
cellulitis at injection site | esophagitis | alopecia
skin ulceration | chest pain | anaphylaxis (see WARNINGS)
urinary retention | pericarditis | allergic edema
renal dysfunction | bowel necrosis | pruritis
neuritis | abdominal pain | shortness of breath
neural toxicity | pancreatitis | urticaria
 | freckling | headache
 | jaundice | sinus bradycardia

Experimental Doses

Severe and at times fatal CNS, GI and pulmonary toxicity (different from that seen with conventional therapy regimens of cytarabine injection) has been reported following some experimental dose schedules of cytarabine injection. These reactions include reversible corneal toxicity and hemorrhagic conjunctivitis, which may be prevented or diminished by prophylaxis with a local corticosteroid eye drop; cerebral and cerebellar dysfunction, including personality changes, somnolence and coma, usually reversible; severe gastrointestinal ulceration, including pneumatosis cystoides intestinalis leading to peritonitis; sepsis and liver abscess; pulmonary edema, liver damage with increased hyperbilirubinemia; bowel necrosis; and necrotizing colitis. Rarely, severe skin rash, leading to desquamation has been reported. Complete alopecia is more commonly seen with experimental high dose therapy than with standard treatment programs using cytarabine. If experimental high dose therapy is used, do not use a preparation containing benzyl alcohol.

Cases of cardiomyopathy with subsequent death have been reported following experimental high dose therapy with cytarabine in combination with cyclophosphamide when used for bone marrow transplant preparation. This cardiac toxicity may be schedule dependent.

A syndrome of sudden respiratory distress, rapidly progressing to pulmonary edema and radiographically pronounced cardiomegaly has been reported following experimental high dose therapy with cytarabine used for the treatment of relapsed leukemia from one institution in 16/72 patients. The outcome of this syndrome can be fatal.

Two patients with adult acute non-lymphocytic leukemia developed peripheral motor and sensory neuropathies after consolidation with high-dose cytarabine, daunorubicin, and asparaginase. Patients treated with high-dose cytarabine should be observed for neuropathy since dose schedule alterations may be needed to avoid irreversible neurologic disorders.

Ten patients treated with experimental intermediate doses of cytarabine (1 g/m^2) with and without other chemotherapeutic agents (meta-AMSA, daunorubicin, etoposide) at various dose regimes developed a diffuse interstitial pneumonitis without clear cause that may have been related to the cytarabine.

Two cases of pancreatitis have been reported following experimental doses of cytarabine injection and numerous other drugs. Cytarabine injection could have been the causative agent.

OVERDOSAGE

There is no antidote for overdosage of Cytarabine Injection. Doses of 4.5 g/m^2 by intravenous infusion over 1 hour every 12 hours for 12 doses have caused an unacceptable increase in irreversible CNS toxicity and death.

Single doses as high as 3 g/m^2 have been administered by rapid intravenous infusion without apparent toxicity.

DOSAGE AND ADMINISTRATION

Cytarabine Injection is not active orally. The schedule and method of administration varies with the program of therapy to be used. Cytarabine Injection may be given by intravenous infusion or injection, subcutaneously, or intrathecally (preservative free preparation only).

Thrombophlebitis has occurred at the site of drug injection or infusion in some patients, and rarely patients have noted pain and inflammation at subcutaneous injection sites. In most instances, however, the drug has been well tolerated.

Patients can tolerate higher total doses when they receive the drug by rapid intravenous injection as compared with slow infusion. This phenomenon is related to the drug's rapid inactivation and brief exposure of susceptible normal and neoplastic cells to significant levels after rapid injection. Normal and neoplastic cells seem to respond in somewhat parallel fashion to these different modes of administration and no clear-cut clinical advantage has been demonstrated for either.

In the induction therapy of acute non-lymphocytic leukemia, the usual cytarabine dose in combination with other anti-cancer drugs is 100 mg/m^2/day by continuous intravenous infusion (Days 1-7) or 100 mg/m^2 intravenous every 12 hours (Days 1-7).

The literature should be consulted for the current recommendations for use in acute lymphocytic leukemia.

Intrathecal Use in Meningeal Leukemia

Cytarabine injection has been used intrathecally in acute leukemia in doses ranging from 5 mg/m^2 to 75 mg/m^2 of body surface area. The frequency of administration varied from once a day for 4 days to once every 4 days. The most frequently used dose was 30 mg/m^2 every 4 days until cerebrospinal fluid findings were normal, followed by one additional treatment. The dosage schedule is usually governed by the type and severity of central nervous system manifestations and the response to previous therapy.

Cytarabine injection given intrathecally may cause systemic toxicity and careful monitoring of the hematopoietic system is indicated. Modification of other anti-leukemia therapy may be necessary. Major toxicity is rare. The most frequently reported reactions after intrathecal administration were nausea, vomiting and fever; these reactions are mild and self-limiting. Paraplegia has been reported. Necrotizing leukoencephalopathy occurred in 5 children; these patients had also been treated with intrathecal methotrexate and hydrocortisone, as well as by central nervous system radiation. Isolated neurotoxicity has been reported. Blindness occurred in two patients in remission whose treatment had consisted of combination systemic chemotherapy, prophylactic central nervous system radiation and intrathecal cytarabine injection.

When cytarabine injection is administered both intrathecally and intravenously within a few days, there is an increased risk of spinal cord toxicity, however, in serious life-threatening disease, concurrent use of intravenous and intrathecal Cytarabine Injection is left to the discretion of the treating physician.

Focal leukemic involvement of the central nervous system may not respond to intrathecal cytarabine injection and may better be treated with radiotherapy.

Chemical Stability of Infusion Solutions

Chemical stability studies were performed by ultraviolet assay on Cytarabine Injection in infusion solutions. These studies showed that when Cytarabine Injection was added to Water for Injection, 5% Dextrose in Water or Sodium Chloride Injection, 94 to 96 percent of the cytarabine was present after 192 hours storage at room temperature.

Parenteral drugs should be inspected visually for particulate matter and discoloration, prior to administration, whenever solution and container permit. If a precipitate has formed as a result of exposure to low temperatures, redissolve by warming up to 55°C for no longer than 30 minutes, under dry heat conditions, and shake until the precipitate has dissolved. Allow to cool prior to use.

HANDLING AND DISPOSAL

Procedures for proper handling and disposal of anti-cancer drugs should be considered. Several guidelines on this subject have been published.^1-7 There is no general agreement that all of the procedures recommended in the guidelines are necessary or appropriate.

HOW SUPPLIED

Cytarabine Injection is available as follows:

2 g/20 mL (100 mg/mL) in a single dose flip top vial (red cap) packaged individually. NDC No.: 61703-319-22

STORAGE CONDITIONS

Protect from light. Retain in carton until time of use.

Store at 20°C to 25°C (68°F to 77°F) [USP Controlled Room Temperature].

REFERENCES

1. Recommendations for the Safe Handling of Parenteral Antineoplastic Drugs, NIH Publications No. 83-2621. For sale by the Superintendent of Documents, U.S. Government Printing Office, Washington, D.C. 20402.
2. AMA Council Report, Guidelines for Handling Parenteral Antineoplastics, JAMA, 1985; 2.53 (11): 1590-1592.
3. National Study Commission on Cytotoxic Exposure – Recommendations for Handling Cytotoxic Agents. Available from Louis P. Jeffrey, ScD., Chairman, National Study Commission on Cytotoxic Exposure, Massachusetts College of Pharmacy and Allied Health Sciences, 179 Longwood Avenue, Boston, Massachusetts 02115.
4. Clinical Oncological Society of Australia, Guidelines and Recommendations for Safe Handling of Antineoplastic Agents. Med J Australia, 1983; 1:426-428.
5. Jones RB, et al: Safe Handling of Chemotherapeutic Agents: A Report from the Mount Sinai Medical Center. CA-A Cancer Journal of Clinicians, 1983; (Sept/Oct) 258-263.
6. American Society of Hospital Pharmacists Technical Assistance Bulletin on Handling Cytotoxic and Hazardous Drugs. Am J. Hosp. Pharm, 1990; 47:1033-1049.
7. Controlling Occupational Exposure to Hazardous Drugs. (OSHA Work Practice Guidelines), Am J. Health- Syst Pharm, 1996; 53:1669-1685.

Distributed by Hospira, Inc. Lake Forest, IL 60045 USA
GUJ-DRUGS/G/28/1267

LAB-1137-4.0
Revised: 6/2020

PRINCIPAL DISPLAY PANEL - 20 mL Vial Label

20 mL Vial
NDC 61703-319-22

Sterile

Cytarabine Injection

2 g/20 mL

(100 mg/mL)

Rx only

For Intravenous, Intrathecal and
Subcutaneous Use Only
Single Dose Vial
Cytotoxic Agent

PRINCIPAL DISPLAY PANEL - 20 mL Vial Carton

VIAL

Hospira

1 x 20 mL Vial
NDC 61703-319-22

Sterile

Cytarabine
Injection

2 g/20 mL

(100 mg/mL)

Rx only

For Intravenous, Intrathecal
and Subcutaneous Use Only
Single Dose Vial

Cytotoxic Agent